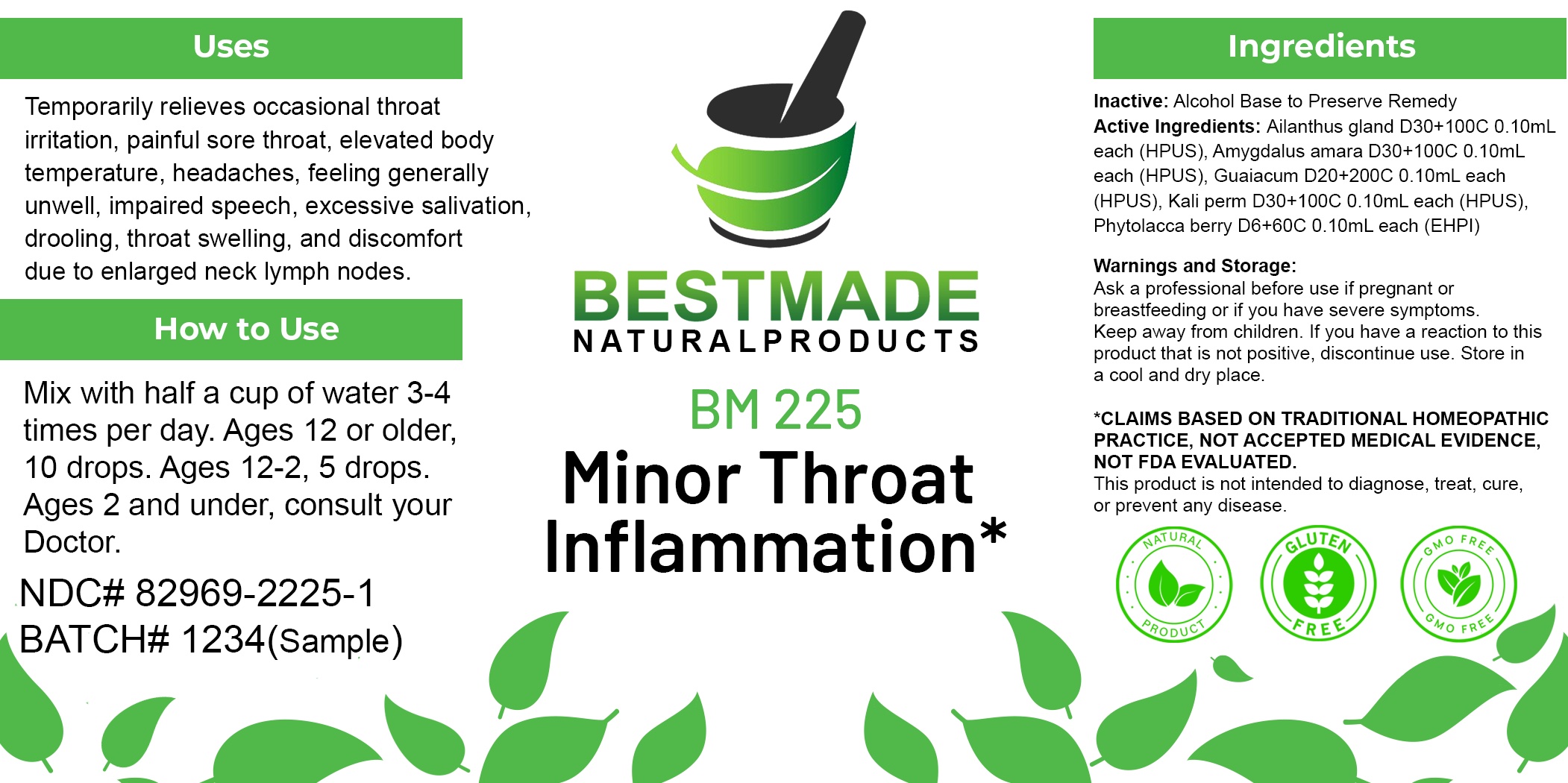 DRUG LABEL: Bestmade Natural Products BM225
NDC: 82969-2225 | Form: LIQUID
Manufacturer: Bestmade Natural Products
Category: homeopathic | Type: HUMAN OTC DRUG LABEL
Date: 20250303

ACTIVE INGREDIENTS: AILANTHUS ALTISSIMA FLOWERING TWIG 30 [hp_C]/30 [hp_C]; PHYTOLACCA AMERICANA FRUIT 30 [hp_C]/30 [hp_C]; POTASSIUM PERMANGANATE 30 [hp_C]/30 [hp_C]; GUAIACUM OFFICINALE RESIN 30 [hp_C]/30 [hp_C]; BITTER ALMOND 30 [hp_C]/30 [hp_C]
INACTIVE INGREDIENTS: ALCOHOL 30 [hp_C]/30 [hp_C]

BM225

DOSAGE AND ADMINISTRATION

How to Use

Mix with half a cup of water 3-4 times per day. Ages 12 or older, 10 drops. Ages 12-2, 5 drops. Ages 2 and under, consult your Doctor.

Inactive:

Alcohol Base to Preserve Product

ACTIVE INGREDIENT

Active Ingredients: Ailanthus gland D30+100C 0.10mL each (HPUS), Amygdalus amara D30+100C 0.10mL each (HPUS), Guaiacum D20+200C 0.10mL each (HPUS), Kali perm D30+100C 0.10mL each (HPUS), Phytolacca berry D6+60C 0.10mL each (EHPI)

KEEP OUT OF REACH OF CHILDREN

Warnings and Storage:

Ask a professional before use if pregnant or breastfeeding or if you have severe symptoms.

Keep away from children. If you have a reaction to this product that is not positive, discontinue use. Store in a cool and dry place

*CLAIMS BASED ON TRADITIONAL HOMEOPATHIC PRACTICE, NOT ACCEPTED MEDICAL EVIDENCE NOT FDA EVALUATED.
This product is not intended to diagnose, treat, cure, or prevent any disease.

Warnings and Storage:

Ask a professional before use if pregnant or breastfeeding or if you have severe symptoms.

Keep away from children. If you have a reaction to this product that is not positive, discontinue use. Store in a cool and dry place

*CLAIMS BASED ON TRADITIONAL HOMEOPATHIC PRACTICE, NOT ACCEPTED MEDICAL EVIDENCE NOT FDA EVALUATED.
This product is not intended to diagnose, treat, cure, or prevent any disease.

Uses
Temporarily relieves occasional throat irritation, painful sore throat, elevated body temperature, headaches, feeling generally unwell, impaired speech, excessive salivation, drooling, throat swelling, and discomfort due to enlarged neck lymph nodes.

Uses
Temporarily relieves occasional throat irritation, painful sore throat, elevated body temperature, headaches, feeling generally unwell, impaired speech, excessive salivation, drooling, throat swelling, and discomfort due to enlarged neck lymph nodes.

Entire package label